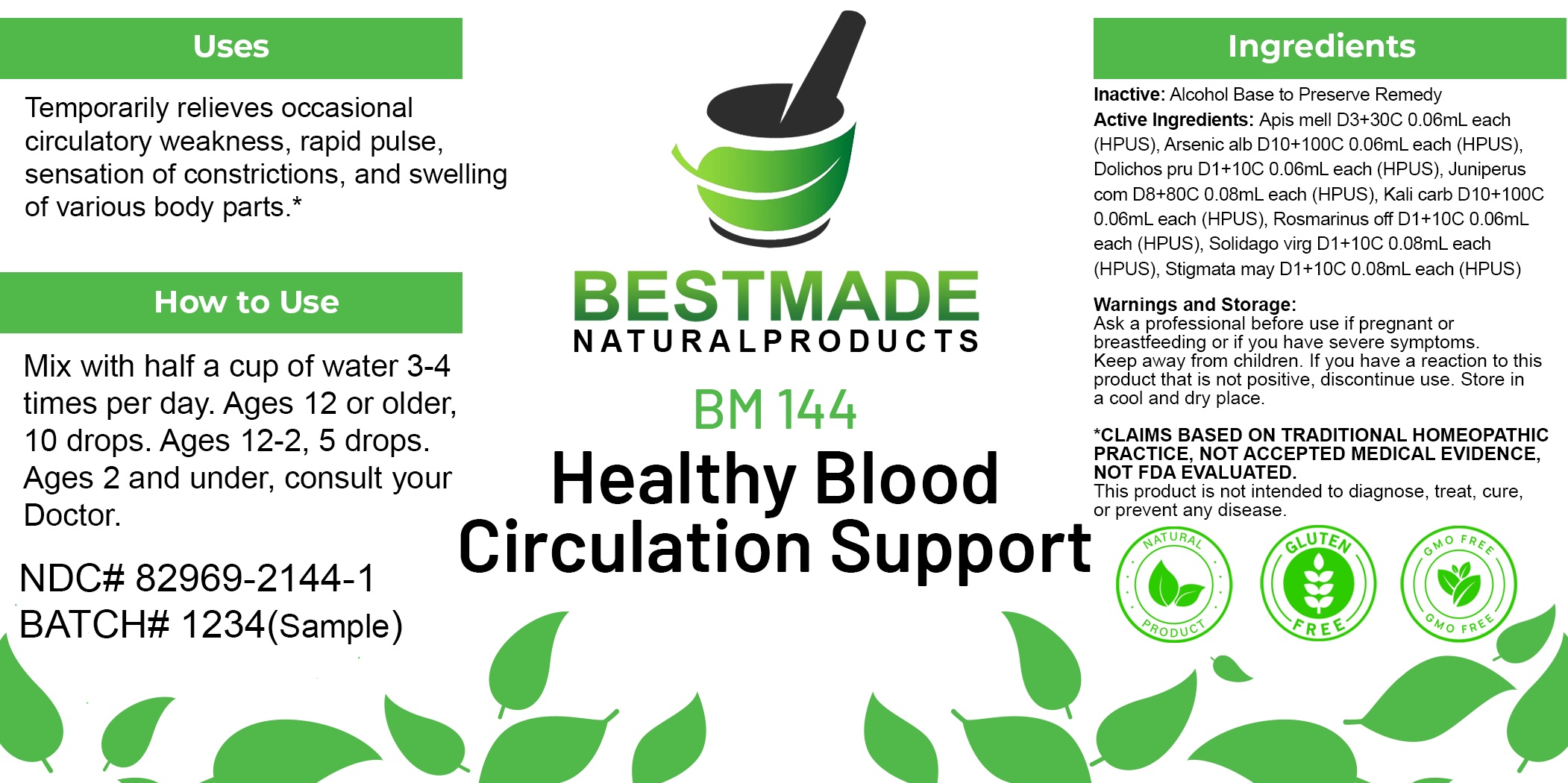 DRUG LABEL: Bestmade Natural Products BM144
NDC: 82969-2144 | Form: LIQUID
Manufacturer: Bestmade Natural Products
Category: homeopathic | Type: HUMAN OTC DRUG LABEL
Date: 20250218

ACTIVE INGREDIENTS: MUCUNA PRURIENS FRUIT TRICHOME 30 [hp_C]/30 [hp_C]; APIS MELLIFERA 30 [hp_C]/30 [hp_C]; JUNIPER BERRY 30 [hp_C]/30 [hp_C]; SOLIDAGO VIRGAUREA FLOWERING TOP 30 [hp_C]/30 [hp_C]; CORN SILK 30 [hp_C]/30 [hp_C]; SALVIA ROSMARINUS FLOWERING TOP 30 [hp_C]/30 [hp_C]; POTASSIUM CARBONATE 30 [hp_C]/30 [hp_C]; ARSENIC TRIOXIDE 30 [hp_C]/30 [hp_C]
INACTIVE INGREDIENTS: ALCOHOL 30 [hp_C]/30 [hp_C]

BM144

DOSAGE AND ADMINISTRATION

How to Use

Mix with half a cup of water 3-4 times per day. Ages 12 or older, 10 drops. Ages 12-2, 5 drops. Ages 2 and under, consult your Doctor.

Inactive:

Alcohol Base to Preserve Product

ACTIVE INGREDIENTS

Apis mell D3+30C 0.06mL each (HPUS), Arsenic alb D10+100C 0.06mL each (HPUS), Dolichos pru D1+10C 0.06mL each (HPUS), Juniperus com D8+80C 0.08mL each (HPUS), Kali carb D10+100C 0.06mL each (HPUS), Rosmarinus off D1+10C 0.06mL each (HPUS), Solidago virg D1+10C 0.08mL each (HPUS), Stigmata may D1+10C 0.08mL each (HPUS)

Uses
Temporarily relieves occasional circulatory weakness, rapid pulse, sensation of constrictions, and swelling of various body parts.*

Uses
Temporarily relieves occasional circulatory weakness, rapid pulse, sensation of constrictions, and swelling of various body parts.*

KEEP OUT OF REACH OF CHILDREN

Warnings and Storage:

Ask a professional before use if pregnant or breastfeeding or if you have severe symptoms.

Keep away from children. If you have a reaction to this product that is not positive, discontinue use. Store in a cool and dry place

*CLAIMS BASED ON TRADITIONAL HOMEOPATHIC PRACTICE, NOT ACCEPTED MEDICAL EVIDENCE NOT FDA EVALUATED.
This product is not intended to diagnose, treat, cure, or prevent any disease.

Warnings and Storage:

Ask a professional before use if pregnant or breastfeeding or if you have severe symptoms.

Keep away from children. If you have a reaction to this product that is not positive, discontinue use. Store in a cool and dry place

*CLAIMS BASED ON TRADITIONAL HOMEOPATHIC PRACTICE, NOT ACCEPTED MEDICAL EVIDENCE NOT FDA EVALUATED.
This product is not intended to diagnose, treat, cure, or prevent any disease.

Entire package label